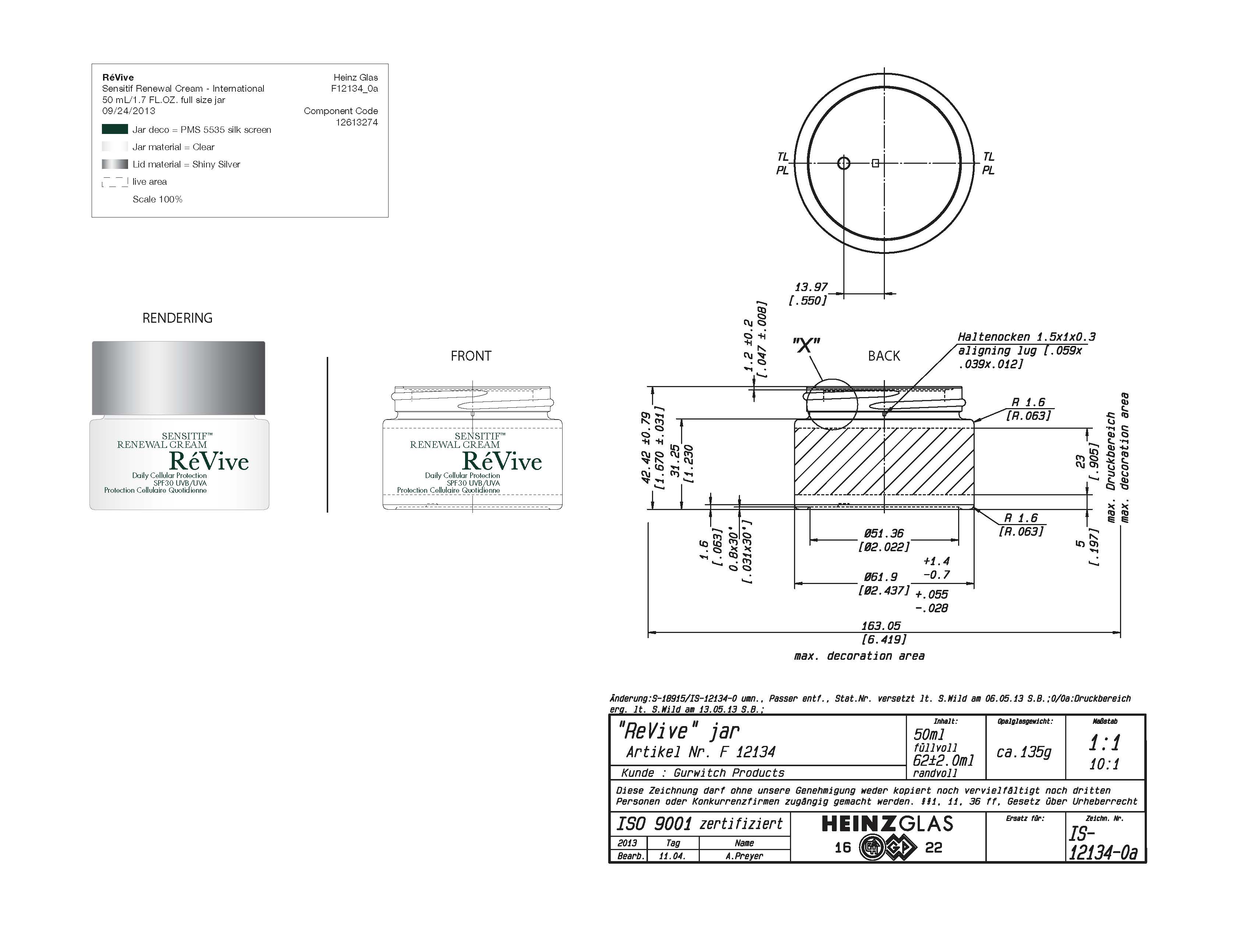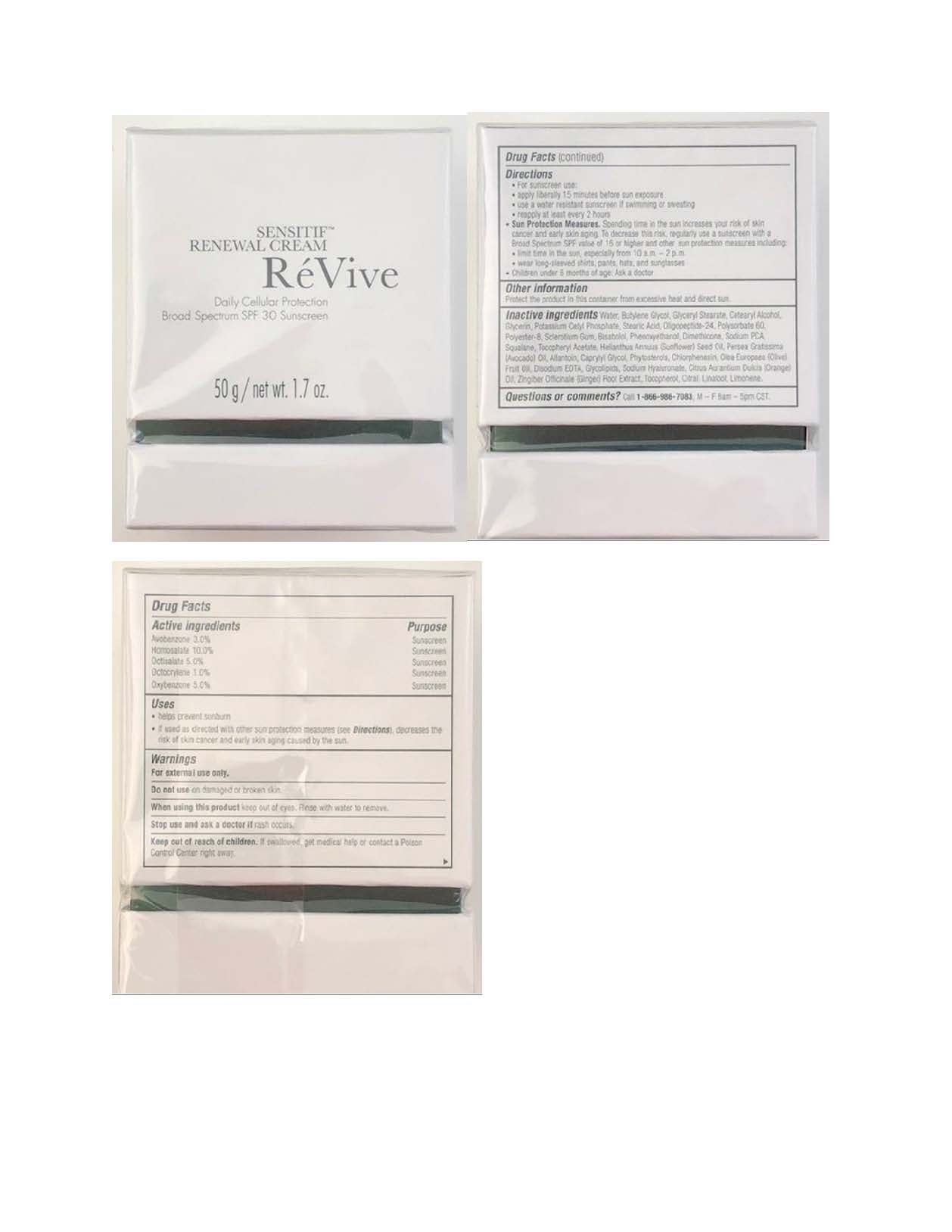 DRUG LABEL: Moisturizer
NDC: 61354-041 | Form: CREAM
Manufacturer: Oxygen Development LLC
Category: otc | Type: HUMAN OTC DRUG LABEL
Date: 20220104

ACTIVE INGREDIENTS: OCTOCRYLENE 1 g/100 g; AVOBENZONE 3 g/100 g; HOMOSALATE 10 g/100 g; OXYBENZONE 5 g/100 g; OCTISALATE 5 g/100 g
INACTIVE INGREDIENTS: CETOSTEARYL ALCOHOL 1.2 g/100 g; SQUALANE 0.5 g/100 g; GLYCERYL MONOSTEARATE 1.75 g/100 g; BUTYLENE GLYCOL 3 g/100 g; POTASSIUM CETYL PHOSPHATE 1 g/100 g; GLYCERIN 0.99 g/100 g; LEVOMENOL 0.64 g/100 g; WATER 59.89 g/100 g; STEARIC ACID 1 g/100 g; BETASIZOFIRAN 0.7 g/100 g; PHENOXYETHANOL 0.64 g/100 g; .ALPHA.-TOCOPHEROL ACETATE 0.5 g/100 g; DIMETHICONE 0.5 g/100 g; POLYESTER-8 (1400 MW, CYANODIPHENYLPROPENOYL CAPPED) 0.75 g/100 g; POLYSORBATE 60 0.8 g/100 g

Revive Sensitif Renewal Daily Cellular Protection Broad Spectrum Spf 30 Sunscreen

Ative ingredients

Avobenzone 3.0%. Hosmosalate 10.0%. Octisalate 5.0%. Octocrylene 1.0%. Oxybenzone 5.0%

Purpose

Sunscreen

Uses

Helps prevent sunburn. If used as directed with other sun protection measures (see Directions), decreases the risk of skin cancer and early skin again caused by the sun

Warnings

For external use only

Do not use on damage or broken skin

When using this product keep out of eyes. Rinse with water to remove.

Stop use and ask a doctor if rash occurs

Keep out of reach of children

If swallowed, get medical help or contact a Poison Control Center rigth away

Directions

For sunscreen use: apply liberally 15 minutes before sun exposure. Use a water resistant sunscreen if swimming or sweating. Reapply at least every 2 hours.

Sun protections measures. Spending time in the sun increasses your risk of skin cancer and early skin aging. To decrease this risk, regulary use a sunscreen with a Broad Spectrum SPF value of 15 or higher and other sun protection measures including: limit time in the sun. especially from 10 a.m - 2 p.m. Wear long - sleeved shirts, pants, hats, and sunglasses. Children under 6 months of age: Ask a doctor.

Other information

Protect the product in this container from excessive heat and direct sun

Inactive ingredients

Water, Butylene Glycol, Glyceryl Stearate, Cetearyl Alcohol, Glycerin, Potassium Cetyl Phosphate, Stearic Acid, Oligopeptide-24, Polysorbate 60, Polyester-8, Sclerotium gum, Bisabolol, Phenoxyethanol, Dimethicone, Sodium PCA, Squalane, Tocopheryl Acetate, Helianthus Annuus (Sunflower) Seed Oil, Persea Gratissima (Avocado) Oil, Allantoin, Caprylyl Glycol, Phytosterols, Chlorphenesin, Olea Europaea (Olive) Fruit Oil, Disodium EDTA, Glycolipids, Sodium Hyaluronate, Citrus Aurantium Dulcis (Orange) Oil, Zingiber Officinale (Ginger) Root Extract, Tocopherol, Citral, Linalool, Limonene.